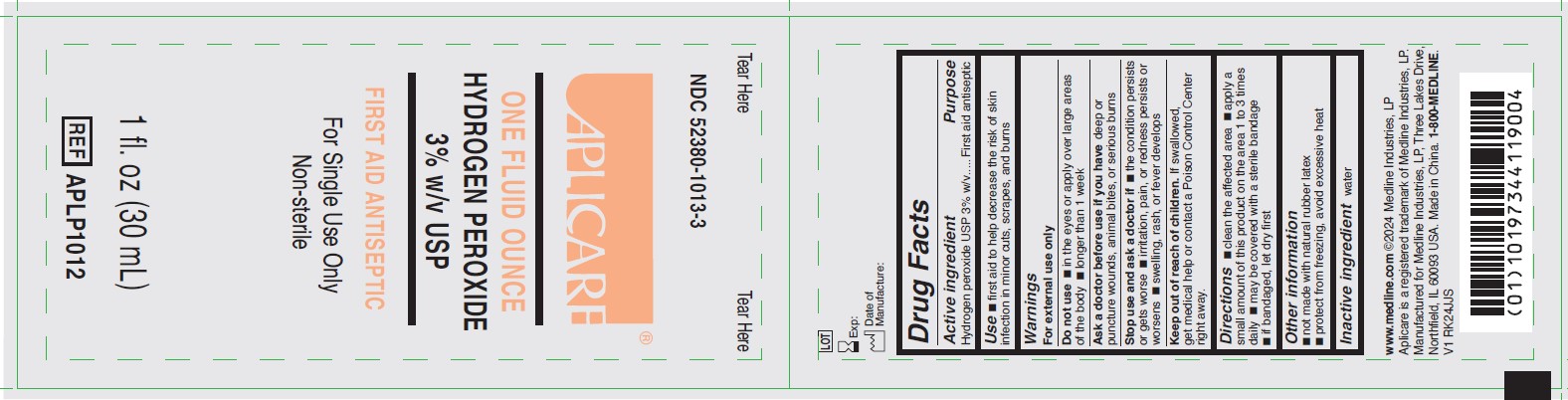 DRUG LABEL: Aplicare
NDC: 52380-1013 | Form: SOLUTION
Manufacturer: Aplicare Products LLC
Category: otc | Type: HUMAN OTC DRUG LABEL
Date: 20250418

ACTIVE INGREDIENTS: HYDROGEN PEROXIDE 3 mL/100 mL
INACTIVE INGREDIENTS: WATER

1013 Aplicare Hydrogen Peroxide 3% Solution

Active Ingredient

Hydrogen peroxide USP 3% w/v

Purpose

First aid antiseptic

Use

- first aid to help decrease the risk of skin infection in minor cuts, scrapes, and burns

Warnings

For external use only

Do not use

- in the eyes or apply over large areas of the body
- longer than 1 week

Ask a doctor before use if you have

deep or puncture wounds, animal bites, or serious burns

Stop use and ask a doctor if

- the condition persists or gets worse
- irritation, pain, or redness persists or worsens
- swelling, rash, or fever develops

Keep out of reach of children.

If swallowed, get medical help or contact a Poison Control Center right away.

Directions

- clean the affected area
- apply a small amount of this product on the area 1 to 3 times daily
- may be covered with a sterile bandage
- if bandaged, let dry first

Other information

- not made with natural rubber latex
- protect from freezing, avoid excessive heat

Inactive ingredient

water

Manufacturing Information

www.medline.com ©2024 Medline Industries, LP
Aplicare is a registered trademark of Medline Industries, LP.
Manufactured for Medline Industries, LP, Three Lakes Drive, Northfield, IL 60093 USA

1-800- MEDLINE.

Made in China. V1 RK24JJS